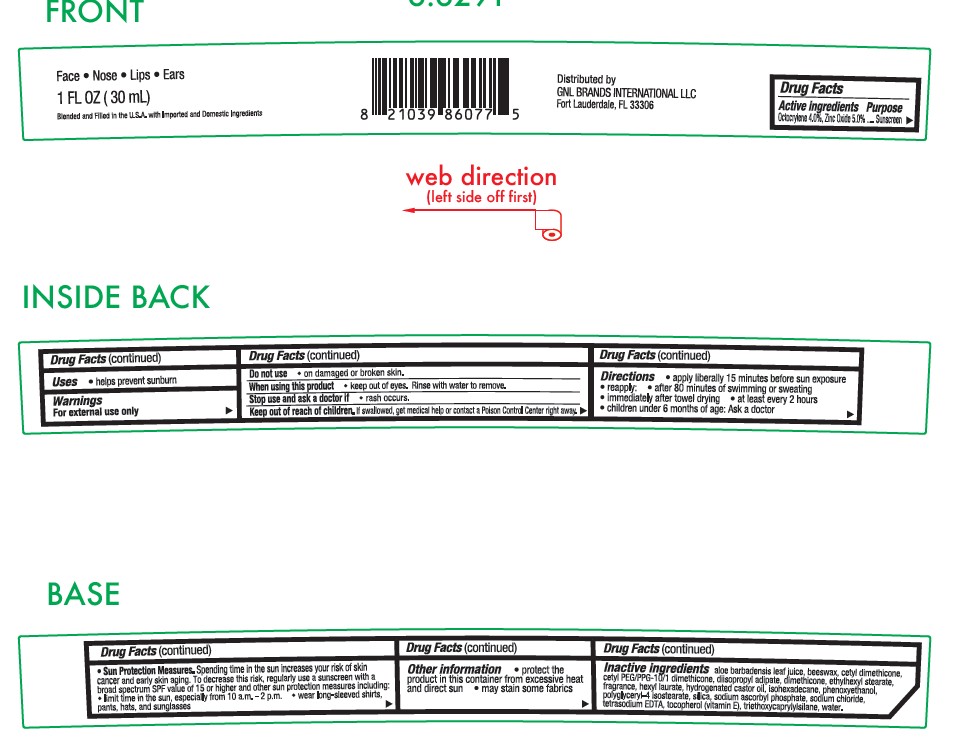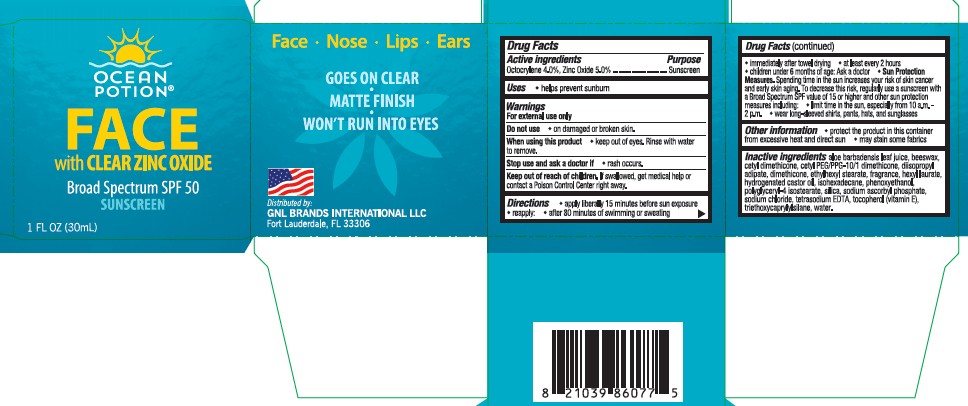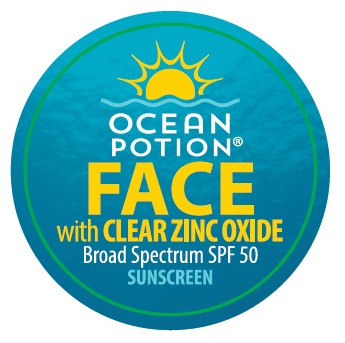 DRUG LABEL: Ocean Potion Face with Clear Zinc Oxide Broad Spectrum SPF 50 Sunscreen
NDC: 85638-006 | Form: LOTION
Manufacturer: GNL BRANDS INTERNATIONAL, LLC
Category: otc | Type: HUMAN OTC DRUG LABEL
Date: 20250815

ACTIVE INGREDIENTS: ZINC OXIDE 50.2125 mg/1 mL; OCTOCRYLENE 40 mg/1 mL
INACTIVE INGREDIENTS: POLYGLYCERYL-4 ISOSTEARATE; SODIUM CHLORIDE; EDETATE SODIUM; CETYL PEG/PPG-10/1 DIMETHICONE (HLB 5); TRIETHOXYCAPRYLYLSILANE; HEXYL LAURATE; ETHYLHEXYL STEARATE; CETYL DIMETHICONE 25; SODIUM ASCORBYL PHOSPHATE; ALOE VERA LEAF; SILICON DIOXIDE; YELLOW WAX; HYDROGENATED CASTOR OIL; ISOHEXADECANE; DIISOPROPYL ADIPATE; WATER; PHENOXYETHANOL; DIMETHICONE; TOCOPHEROL

Ocean Potion Face with Clear Zinc Oxide Broad Spectrum SPF 50 Sunscreen

Active ingredients

Octocrylene 4.0%, Zinc Oxide 5.0%

Purpose

Sunscreen

Uses

- helps prevent sunburn
- if used as directed with other sun protection measures (see Directions), decreases the risk of skin cancer and early aging caused by the sun

Warnings

For external use only

Do not use

• on damaged or broken skin.

When using this product

• keep out of eyes. Rinse with water to remove.

Stop use and ask a doctor if

• rash occurs.

Keep out of reach of children.

If swallowed, get medical help or contact a Poison Control Center right away.

Directions

- apply liberally 15 minutes before sun exposure.
- reapply:
- after 80 minutes of swimming or sweating
- immediately after towel drying
- at least every 2 hours
- children under 6 months of age: Ask a doctor
- Sun Protection Measures. Spending time in the sun increases your risk of skin cancer and early skin aging. To decrease this risk, regularly use a sunscreen with a Broad Spectrum SPF value of 15 or higher and other sun protection measures including:
- limit time in the sun especially from 10 a.m. – 2 p.m.
- wear long-sleeved shirts, pants, hats, and sunglasses

Other information

- protect the product in this container from excessive heat and direct sun
- may stain or damage some fabrics, materials or surfaces

Inactive ingredients

water, ethylhexyl stearate, diisopropyl adipate, cetyl dimethicone, polyglyceryl-4 isostearate, cetyl PEG/PPG-10/1 dimethicone, hexyl laurate, phenoxyethanol, beeswax, isohexadecane, hydrogenated castor oil, fragrance, silica, triethoxycaprylylsilane, dimethicone, tocopherol (Vitamin E), tetrasodium EDTA, aloe barbadensis leaf juice, sodium chloride, sodium ascorbyl phosphate.